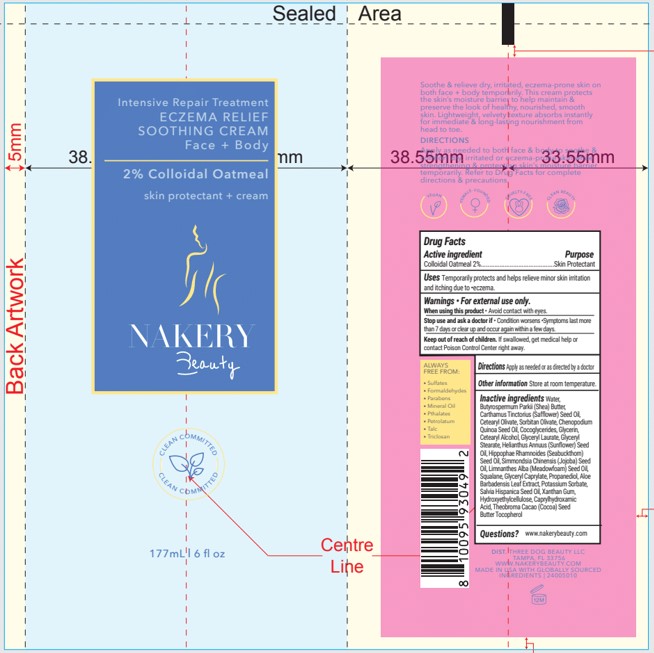 DRUG LABEL: ECZEMA RELIEF SOOTHING
NDC: 83092-105 | Form: CREAM
Manufacturer: Three Dog Beauty LLC
Category: otc | Type: HUMAN OTC DRUG LABEL
Date: 20221103

ACTIVE INGREDIENTS: OATMEAL 2 g/100 mL
INACTIVE INGREDIENTS: HYDROXYETHYL CELLULOSE, UNSPECIFIED; COCOA BUTTER; CAPRYLHYDROXAMIC ACID; SAFFLOWER OIL; SALVIA HISPANICA SEED; XANTHAN GUM; GLYCERYL CAPRYLATE; POTASSIUM SORBATE; SHEA BUTTER; CETEARYL OLIVATE; SORBITAN OLIVATE; CHENOPODIUM QUINOA SEED; COCO-GLYCERIDES; CETOSTEARYL ALCOHOL; GLYCERYL LAURATE; GLYCERYL MONOSTEARATE; SUNFLOWER OIL; TOCOPHEROL; JOJOBA OIL; HIPPOPHAE RHAMNOIDES SEED OIL; GLYCERIN; WATER; MEADOWFOAM SEED OIL; SQUALANE; PROPANEDIOL; ALOE VERA LEAF

THREE DOG BEAUTY - NAKERY BEAUTY - ECZEMA RELIEF SOOTHING CREAM (83092-105)

ACTIVE INGREDIENT

COLLOIDAL OATMEAL 2%

PURPOSE

SKIN PROTECTANT

USES

TEMPORARILY PROTECTS AND HELPS RELIEVE MINOR SKIN IRRITATION AND ITCHING DUE TO ECZEMA.

WARNINGS

- FOR EXTERNAL USE ONLY.

WHEN USING THIS PRODUCT

- AVOID CONTACT WITH EYES.

STOP USE AND ASK A DOCTOR IF

- CONDITION WORSENS
- SYMPTOMS LAST MORE THAN 7 DAYS OR CLEAR UP AND OCCUR AGAIN WITHIN A FEW DAYS.

KEEP OUT OF REACH OF CHILDREN. IF SWALLOWED, GET MEDICAL HELP OR CONTACT POISON CONTROL CENTER RIGHT AWAY.

DIRECTIONS

APPLY AS NEEDED OR AS DIRECTED BY A DOCTOR.

OTHER INFORMATION

STORE AT ROOM TEMPERATURE.

INACTIVE INGREDIENTS

WATER, BUTYROSPERMUM PARKII (SHEA) BUTTER, CARTHAMUS TINCTORIUS (SAFFLOWER) SEED OIL, CETEARYL OLIVATE, SORBITAN OLIVATE, CHENOPODIUM QUINOA SEED OIL, COCOGLYCERIDES, GLYCERIN, CETEARYL ALCOHOL, GLYCERYL LAURATE, GLYCERYL STEARATE, HELIANTHUS ANNUUS (SUNFLOWER) SEED OIL, HIPPOPHAE RHAMNOIDES (SEABUCKTHORN) SEED OIL, SIMMONDSIA CHINENSIS (JOJOBA) SEED OIL, LIMNANTHES ALBA (MEADOWFOAM) SEED OIL, SQUALANE, GLYCERYL CAPRYLATE, PROPANEDIOL, ALOE BARBADENSIS LEAF EXTRACT, POTASSIUM SORBATE, SALVIA HISPANICA SEED OIL, XANTHAN GUM, HYDROXYETHYLCELLULOSE, CAPRYLHYDROXAMIC ACID, THEOBROMA CACOA (COCOA) SEED BUTTER, TOCOPHEROL

QUESTIONS?

WWW.NAKERYBEAUTY.COM